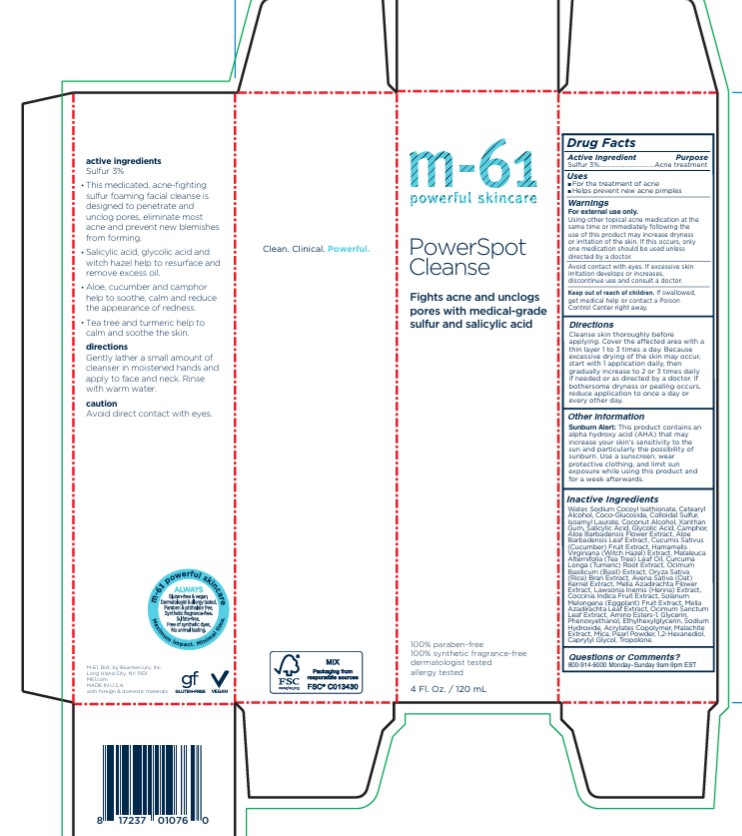 DRUG LABEL: PowerSpot Cleanse
NDC: 72203-014 | Form: SOAP
Manufacturer: Bluemercury
Category: otc | Type: HUMAN OTC DRUG LABEL
Date: 20251209

ACTIVE INGREDIENTS: SULFUR 30 mg/1 mL
INACTIVE INGREDIENTS: ETHYLHEXYLGLYCERIN; SODIUM HYDROXIDE; BUTYL ACRYLATE/METHYL METHACRYLATE/METHACRYLIC ACID COPOLYMER (18000 MW); MICA; PEARL (HYRIOPSIS CUMINGII); WATER; SODIUM COCOYL ISETHIONATE; CETOSTEARYL ALCOHOL; COCO GLUCOSIDE; ISOAMYL LAURATE; COCONUT ALCOHOL; XANTHAN GUM; SALICYLIC ACID; GLYCOLIC ACID; ALOE VERA FLOWER; ALOE VERA LEAF; CUCUMBER; HAMAMELIS VIRGINIANA TOP; TEA TREE OIL; TURMERIC; BASIL; RICE BRAN; OAT; AZADIRACHTA INDICA FLOWER; LAWSONIA INERMIS LEAF; COCCINIA GRANDIS FRUIT; EGGPLANT; AZADIRACHTA INDICA LEAF; HOLY BASIL LEAF; GLYCERIN; PHENOXYETHANOL

PowerSpot Cleanse

Drug Facts

Active Ingredients

Sulfur 3%

Purpose

Acne treatment

Uses

- For the treatment of acne
- Helps keep skin clear of new acne blemishes

Warnings

For external use only.

- Do not get into eyes. If excessive skin irritation develops or increases, discontinue use and consult a doctor.
- Using other topical acne medications at the same time or immediately following use of this product may increase dryness or irritation of the skin. If this occurs, only one medication should be used unless directed by a doctor.

- Keep out of reach of children.If swallowed, get medical help or contact a Poison Control Center right away.

Directions

- Gently lather a small amount of cleanser in moistened hands and apply to face and neck. Rinse with warm water.

Inactive Ingredients

Water (Aqua), Sodium Cocoyl Isethionate, Cetearyl Alcohol, Coco-Glucoside, Colloidal Sulfur, Isoamyl Laurate, Coconut Alcohol, Xanthan Gum, Salicylic Acid, Glycolic Acid, Camphor, Aloe Barbadensis Flower Extract, Aloe Barbadensis Leaf Extract, Cucumis Sativus (Cucumber) Fruit Extract, Hamamelis Virginiana (Witch Hazel) Extract, Melaleuca Alternifolia (Tea Tree) Leaf Oil, Curcuma Longa (Tumeric) Root Extract, Ocimum Basilicum (Basil) Extract, Oryza Sativa (Rice) Bran Extract, Avena Sativa (Oat) Kernel Extract, Melia Azadirachta Flower Extract, Lawsonia Inermis (Henna) Extract, Coccinia Indica Fruit Extract, Solanum Melongena (Eggplant) Fruit Extract, Melia Azadirachta Leaf Extract, Ocimum Sanctum Leaf Extract, Amino Esters-1, Glycerin, Phenoxyethanol, Ethylhexylglycerin, Sodium Hydroxide, Acrylates Copolymer, Malachite Extract, Mica, Pearl Powder

PRINCIPAL DISPLAY PANEL - 120 mL Tube Carton

m-61®
powerful skincare

PowerSpot
Cleanse

CLARIFYING
3% SULFUR
ACNE TREATMENT
FACE CLEANSER

Blemish-fighting
and clarifying
foaming cleanser
with salicylic acid,
tea tree & cucumber

combination / blemish-prone skin

100% paraben-free
100% synthetic fragrance-free
dermatologist tested
allergy tested

120 mL e 4 FL. OZ.